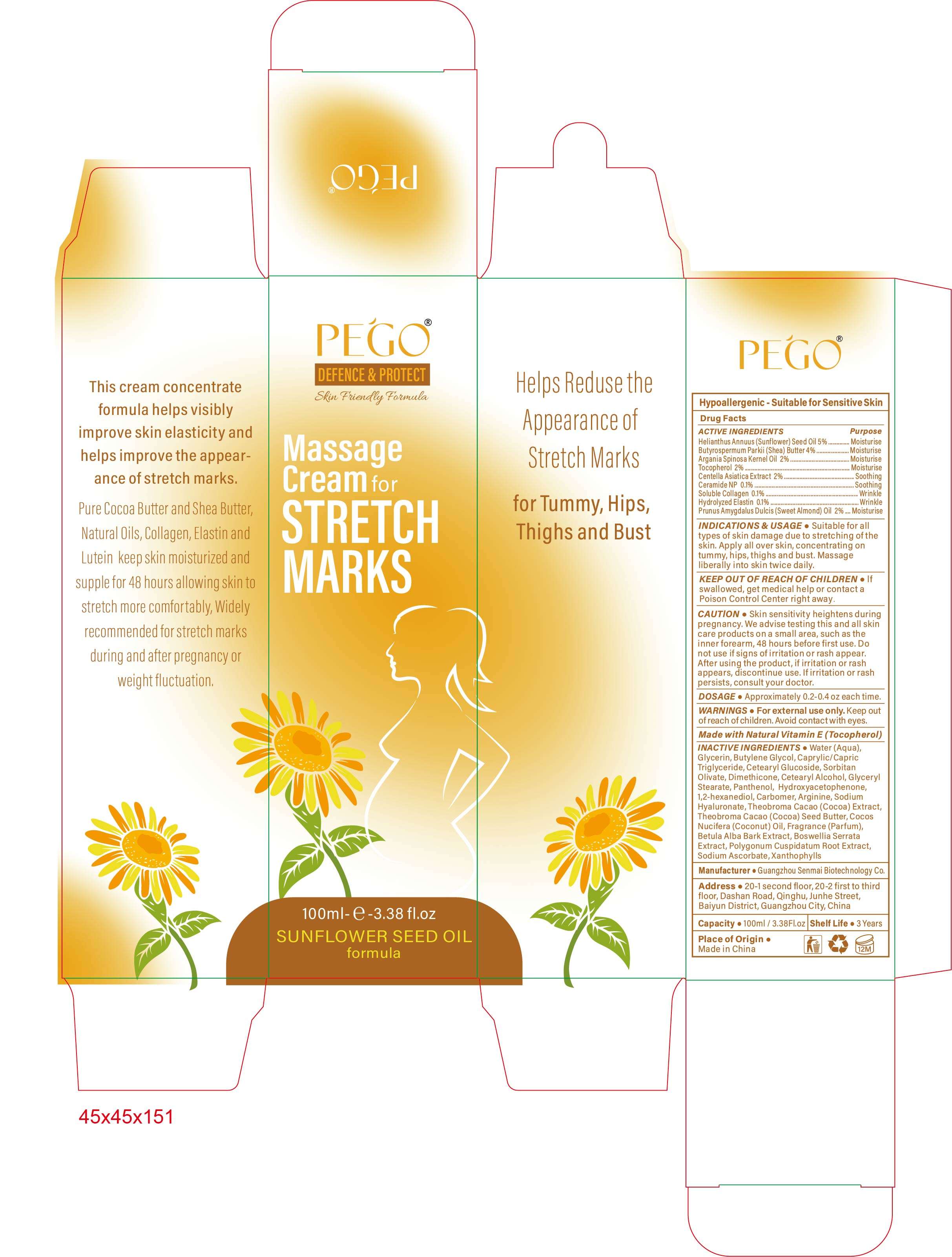 DRUG LABEL: Massage cream for stretch marks
NDC: 84509-005 | Form: CREAM
Manufacturer: Guangzhou Senmai Biotechnology Co.
Category: otc | Type: HUMAN OTC DRUG LABEL
Date: 20250108

ACTIVE INGREDIENTS: COLLAGEN, SOLUBLE, FISH SKIN 100 mg/100 mL; SUNFLOWER OIL 5000 mg/100 mL; ALMOND OIL 2000 mg/100 mL; HYDROLYZED BOVINE ELASTIN (BASE; 1000 MW) 100 mg/100 mL; SHEA BUTTER 4000 mg/100 mL; ARGAN OIL 2000 mg/100 mL; TOCOPHEROL 2000 mg/100 mL; CENTELLA ASIATICA TRITERPENOIDS 2000 mg/100 mL; CERAMIDE NP 100 mg/100 mL
INACTIVE INGREDIENTS: WATER; BUTYLENE GLYCOL; CARBOMER 1342; INDIAN FRANKINCENSE; CETOSTEARYL ALCOHOL; HYALURONATE SODIUM; BETULA PUBESCENS BARK; COCOA; REYNOUTRIA JAPONICA ROOT; LUTEIN; HYDROXYACETOPHENONE; ARGININE; DIMETHICONE; COCOA BUTTER; 1,2-HEXANEDIOL; MEDIUM-CHAIN TRIGLYCERIDES; FRAGRANCE 13576; SODIUM ASCORBATE; CETEARYL GLUCOSIDE; SORBITAN OLIVATE; GLYCERYL MONOSTEARATE; PANTHENOL; COCONUT OIL; GLYCERIN

DESCRIPTION

Hypoallergenic-Suitable for Sensitive Skin

Active Ingredients

Helianthus Annuus (Sunflower) Seed 0il 5%
Butyrospermum Parkii (Shea) Buter 4%
Argania Spinosa Kernel 0il 2%
Tocopherol 2%
Centella Asiatica Extract 2%
Ceramide NP 0.1%
Soluble Collagen 0.1%
Hydrolyzed Elastin 0.1%
Prunus Amygdalus Dulcis (Sweet Almond) Oil 2%

Purpose

Moisturise,Soothing,Wrinkle

INDICATIONS& USAGE

Suitable for all types of skin damage due to stretching of the skin. Apply all over skin, concentrating on tummy, hips, thighs and bust.Massage liberally into skin twice daily.

KEEP OUT OF REACH OF CHILDREN

lf swallowed, get medical help or contact a Poison Control Center right away.

CAUTION

Skin sensitivity heightens during pregnancy. We advise testing this and all skin care products on a small area, such as the inner forearm,48 hours before first use. Do not use if signs of irritation or rash appear. After using the product, if irritation or rash appears, discontinue use. lf irritation or rash persists, consult your doctor.

DOSAGE

Approximately 0.2-0.4 oz each time.

Warnings

For external use only. Keep out ofreach of children.Avoid contact with eyes.

DESCRIPTION

Made with Natural Vitamin E (Tocopherol)

Inactive Ingredients

Water (Aqua), Glycerin,Butylene Glycol,Caprylic/Capric Triglyceride,Cetearyl Glucoside,Sorbitan Olivate, Dimethicone,
Cetearyl Alcohol,Glyceryl Stearate,Panthenol,Hydroxyacetophenone,1,2-hexanediol, Carbomer,Arginine, Sodium Hyaluronate,
Theobroma Cacao (Cocoa) Extract, Theobroma Cacao(Cocoa) Seed Butter,Cocos Nucifera (Coconut) Oil, Fragrance(Parfum),
Betula Alba Bark Extract, Boswellia Serrata Extract,Polygonum Cuspidatum Root Extract,Sodium Ascorbate,Xanthophylls

Manufacturer

Guangzhou Senmai Biotechnology Co.

Address

20-1second floor, 20-2 first to third floor,Dashan Road,Qinghu,Junhe Street, Baiyun district, Guangzhou City, China.

Capacity

100ml/3.38Fl.oz

Shelf Life

3 Years

Place of Origin

Made in China